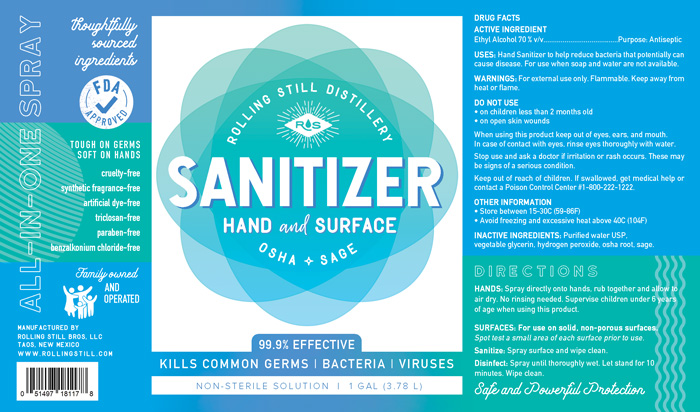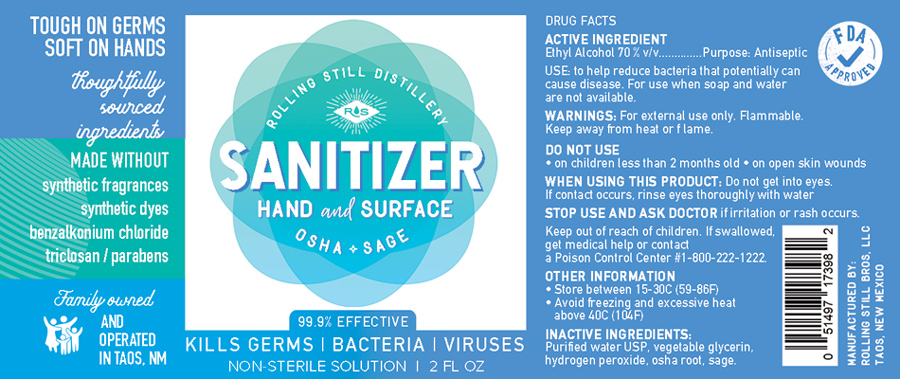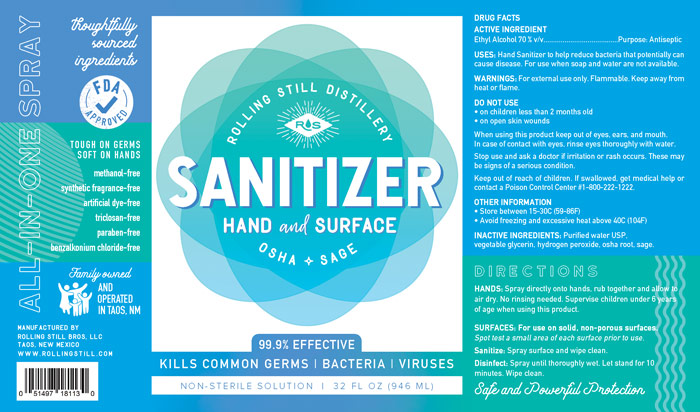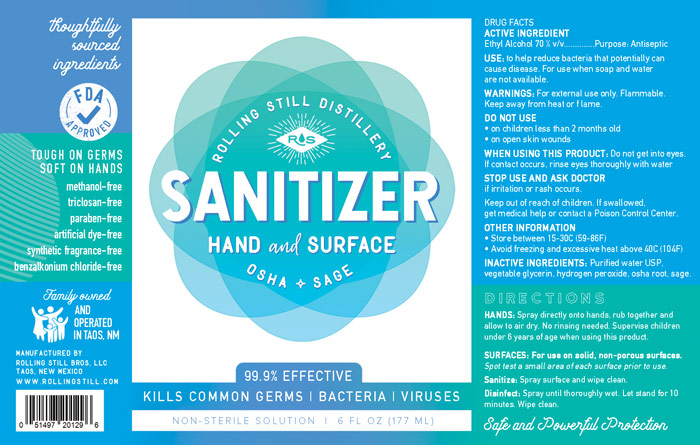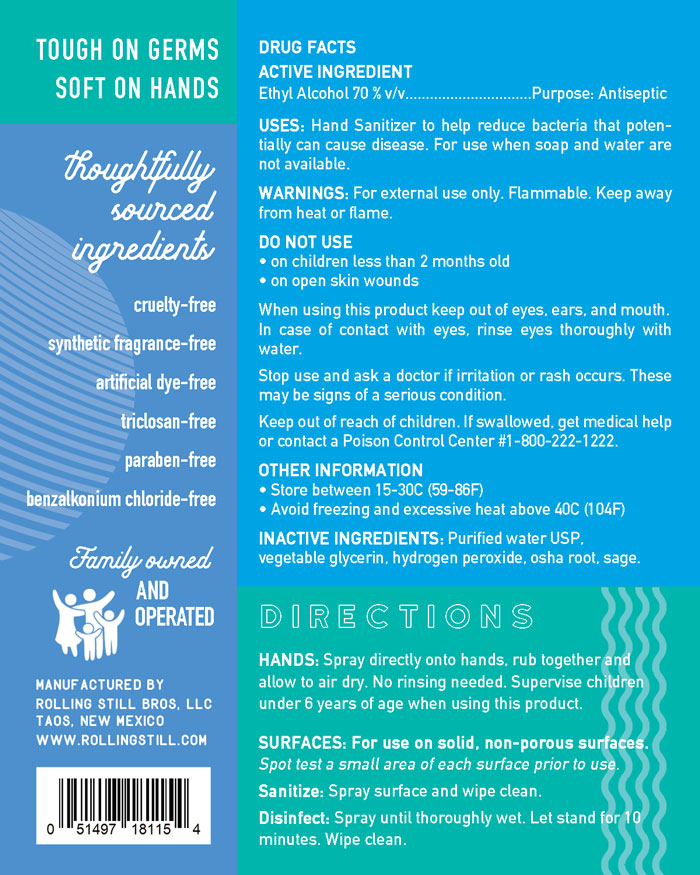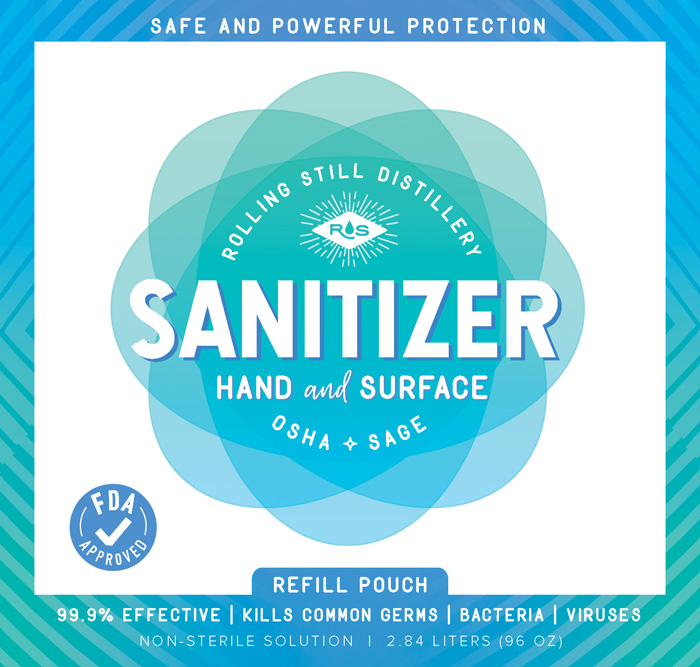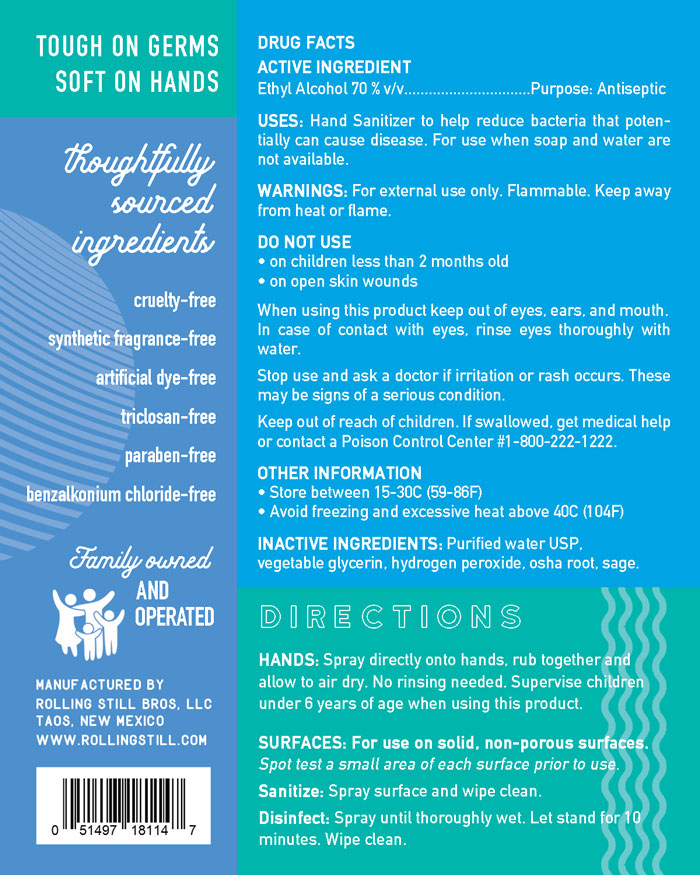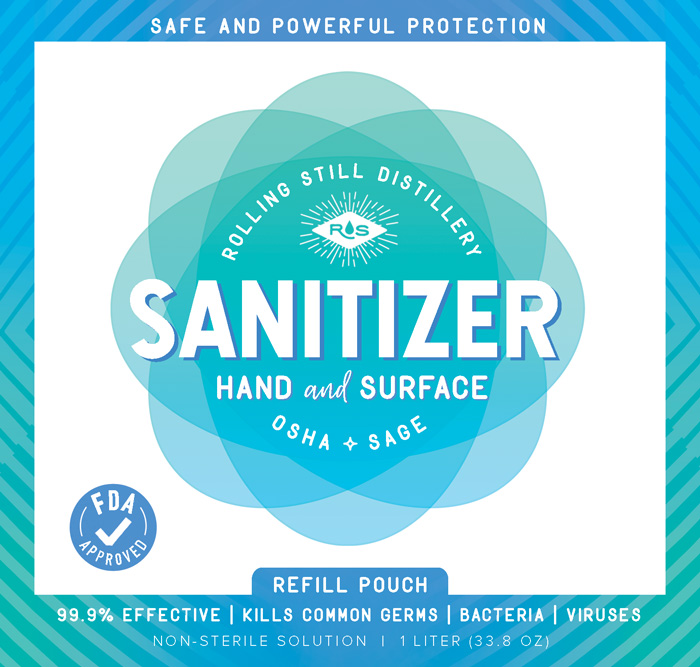 DRUG LABEL: Rolling Still Hand and Surface Sanitizer
NDC: 76581-002 | Form: LIQUID
Manufacturer: Rolling Still Wellness, LLC
Category: otc | Type: HUMAN OTC DRUG LABEL
Date: 20201103

ACTIVE INGREDIENTS: ALCOHOL 0.7 L/1 L
INACTIVE INGREDIENTS: GLYCERIN 0.015 L/1 L; HYDROGEN PEROXIDE 0.00125 L/1 L; WATER; LIGUSTICUM PORTERI ROOT; SAGE

Hand Sanitizer

This is a hand sanitizer manufactured according to the Temporary Policy for Preparation of Certain Alcohol-Based Hand Sanitizer Products During the Public Health Emergency (CoViD-19); Guidance for Industry.

The hand sanitizer is manufactured using only the following United States Pharmacopoeia (USP) grade ingredients in the preparation of the product (percentage in final product formulation) consistent with World Health Organization (WHO) recommendations:

1. Alcohol (ethanol) (USP or Food Chemical Codex (FCC) grade) (70%, volume/volume (v/v)) in an aqueous solution denatured according to Alcohol and Tobacco Tax and Trade Bureau regulations in 27 CFR part 20.
2. Glycerol (1.45% v/v).
3. Hydrogen peroxide (0.125% v/v).
4. Sterile distilled water or boiled cold water.
5. Sage.
6. Osha root.

Active Ingredient(s)

Alcohol 70% v/v. Purpose: Antiseptic

Purpose

Antiseptic, Hand Sanitizer

Use

Hand Sanitizer to help reduce bacteria that potentially can cause disease. For use when soap and water are not available.

Warnings

For external use only. Flammable. Keep away from heat or flame

Do not use

- in children less than 2 months of age
- on open skin wounds

When using this product keep out of eyes, ears, and mouth. In case of contact with eyes, rinse eyes thoroughly with water.
Stop use and ask a doctor if irritation or rash occurs. These may be signs of a serious condition.
Keep out of reach of children. If swallowed, get medical help or contact a Poison Control Center right away.

Stop use and ask a doctor if irritation or rash occurs. These may be signs of a serious condition.

Keep out of reach of children. If swallowed, get medical help or contact a Poison Control Center right away.

Directions

Spray directly onto hands, rub together and allow to air dry. No rinsing needed. Supervise children under 6 years of age when using this product.

RECENT MAJOR CHANGES

Spray directly onto hands, rub together and allow to air dry. No rinsing necessary. Supervise children under the age of 6 when using this product.

06/01/2020

Other information

- Store between 15-30C (59-86F)
- Avoid freezing and excessive heat above 40C (104F)

Inactive ingredients

glycerin, hydrogen peroxide, purified water USP, sage, osha root

Package Label - Principal Display Panel

3.79 L NDC: 76581-001-01

2.84 L NDC: 76581-001-06

.95 L NDC: 76581-001-04

1 L NDC: 76581-001-03

.06 L NDC: 76581-001-02

0.177L NDC: 76581-002-07